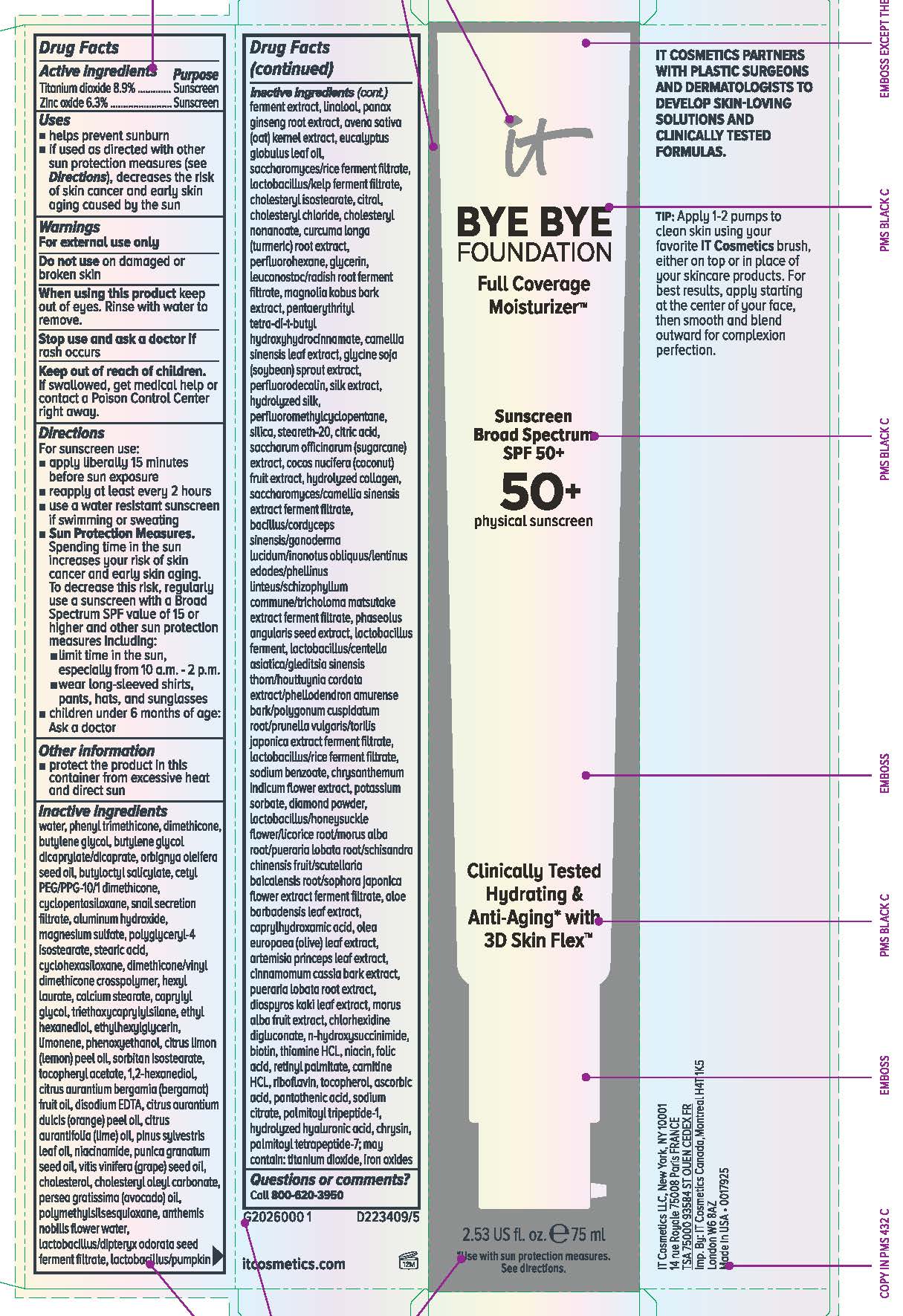 DRUG LABEL: it cosmetics Bye Bye Foundation Full Coverage Moisturizer  Broad Spectrum 50 Plus Sunscreen All Shades
NDC: 69259-2888 | Form: LOTION
Manufacturer: IT COSMETICS, LLC
Category: otc | Type: HUMAN OTC DRUG LABEL
Date: 20231230

ACTIVE INGREDIENTS: TITANIUM DIOXIDE 89 mg/1 mL; ZINC OXIDE 63 mg/1 mL
INACTIVE INGREDIENTS: WATER; PHENYL TRIMETHICONE; DIMETHICONE; BUTYLENE GLYCOL; BUTYLENE GLYCOL DICAPRYLATE/DICAPRATE; BABASSU OIL; BUTYLOCTYL SALICYLATE; CETYL PEG/PPG-10/1 DIMETHICONE (HLB 2); CYCLOMETHICONE 5; ALUMINUM HYDROXIDE; MAGNESIUM SULFATE, UNSPECIFIED FORM; POLYGLYCERYL-4 ISOSTEARATE; STEARIC ACID; CYCLOMETHICONE 6; DIMETHICONE/VINYL DIMETHICONE CROSSPOLYMER (HARD PARTICLE); HEXYL LAURATE; CALCIUM STEARATE; CAPRYLYL GLYCOL; TRIETHOXYCAPRYLYLSILANE; ETHOHEXADIOL; ETHYLHEXYLGLYCERIN; LIMONENE, (+)-; PHENOXYETHANOL; LEMON OIL; SORBITAN ISOSTEARATE; .ALPHA.-TOCOPHEROL ACETATE; 1,2-HEXANEDIOL; BERGAMOT OIL; EDETATE DISODIUM; ORANGE OIL; LIME OIL; PINE NEEDLE OIL (PINUS SYLVESTRIS); NIACINAMIDE; PUNICA GRANATUM SEED OIL; GRAPE SEED OIL; CHOLESTEROL; CHOLESTERYL OLEYL CARBONATE; AVOCADO OIL; POLYMETHYLSILSESQUIOXANE (4.5 MICRONS); CHAMAEMELUM NOBILE FLOWER OIL; LINALOOL, (+/-)-; ASIAN GINSENG; OAT; EUCALYPTUS OIL; CHOLESTERYL ISOSTEARATE; CITRAL; CHOLESTERYL CHLORIDE; CHOLESTERYL NONANOATE; TURMERIC; PERFLEXANE; GLYCERIN; LEUCONOSTOC/RADISH ROOT FERMENT FILTRATE; MAGNOLIA KOBUS BARK; PENTAERYTHRITOL TETRAKIS(3-(3,5-DI-TERT-BUTYL-4-HYDROXYPHENYL)PROPIONATE); GREEN TEA LEAF; SOYBEAN; PERFLUNAFENE; PERFLUOROMETHYLCYCLOPENTANE; SILICA DIMETHYL SILYLATE; STEARETH-20; CITRIC ACID MONOHYDRATE; SUGARCANE; COCONUT; ADZUKI BEAN; LACTOBACILLUS FERMENTUM; SODIUM BENZOATE; CHRYSANTHEMUM INDICUM FLOWER; POTASSIUM SORBATE; BUTYLATED HYDROXYTOLUENE; DIAMOND; ALOE VERA LEAF; CAPRYLHYDROXAMIC ACID; OLEA EUROPAEA LEAF; ARTEMISIA PRINCEPS LEAF; CHINESE CINNAMON; PUERARIA MONTANA VAR. LOBATA ROOT; DIOSPYROS KAKI LEAF; WHITE MULBERRY; CHLORHEXIDINE GLUCONATE; N-HYDROXYSUCCINIMIDE; BIOTIN; THIAMINE HYDROCHLORIDE; NIACIN; FOLIC ACID; VITAMIN A PALMITATE; LEVOCARNITINE HYDROCHLORIDE; RIBOFLAVIN; TOCOPHEROL; ASCORBIC ACID; PANTOTHENIC ACID; SODIUM CITRATE; PALMITOYL TRIPEPTIDE-1; CHRYSIN; PALMITOYL TETRAPEPTIDE-7; FERRIC OXIDE RED

Drug Facts

Active ingredients

Titanium dioxide 8.9%

Zinc oxide 6.3%

Purpose

Sunscreen

Uses

- helps prevent sunburn

- if used as directed with other sun protection measures (see Directions), decreases the risk of skin cancer and early skin aging caused by the sun

Warnings

For external use only

Do not use

on damaged or broken skin

When using this product

keep out of eyes. Rinse with water to remove.

Stop use and ask a doctor if

rash occurs

Keep out of reach of children.

If swallowed, get medical help or contact a Poison Control Center right away.

Directions

● shake well before use

● apply liberally 15 minutes before sun exposure

● reapply at least every 2 hours

● use a water resistant sunscreen if swimming or sweating

● Sun Protection Measures. Spending time in the sun increases your risk of skin cancer and early skin aging. To decrease this risk,

regularly use a sunscreen with a Broad Spectrum SPF value of 15 or higher and other sun protection measures including:

● limit time in the sun, especially from 10 a.m. – 2 p.m.

● wear long-sleeved shirts, pants, hats, and sunglasses

● children under 6 months of age: Ask a doctor

Other information

protect the product in this container from excessive heat and direct sun

Inactive ingredients

water, phenyl trimethicone, dimethicone, butylene glycol, butylene glycol dicaprylate/dicaprate, orbignya oleifera seed oil, butyloctyl salicylate, cetyl PEG/PPG-10/1 dimethicone, cyclopentasiloxane, snail secretion filtrate, aluminum hydroxide, magnesium sulfate, polyglyceryl-4 isostearate,, stearic acid,, cyclohexasiloxane, dimethicone/vinyl dimethicone crosspolymer, hexyl laurate, calcium stearate, caprylyl glycol, triethoxycaprylylsilane, ethyl hexanediol, ethylhexylglycerin, limonene, phenoxyethanol, citrus limon (lemon) peel oil, sorbitan isostearate, tocopheryl acetate, 1,2-hexanediol, citrus aurantium bergamia (bergamot) fruit oil, disodium EDTA, citrus aurantium dulcis (orange) peel oil, citrus aurantifolia (lime) oil, pinus sylvestris leaf oil, niacinamide, punica granatum seed oil, vitis vinifera (grape) seed oil, cholesterol, cholesteryl oleyl carbonate, persea gratissima (avocado) oil, polymethylsilsesquioxane, anthemis nobilis flower water, lactobacillus/dipteryx odorata seed ferment filtrate, lactobacillus/pumpkin ferment extract, linalool, panax ginseng root extract, avena sativa (oat) kernel extract, eucalyptus globulus leaf oil, saccharomyces/rice ferment filtrate, lactobacillus/kelp ferment filtrate, cholesteryl isostearate, citral, cholesteryl chloride, cholesteryl nonanoate, curcuma longa (turmeric) root extract, perfluorohexane, glycerin, leuconostoc/radish root ferment filtrate, magnolia kobus bark extract, pentaerythrityl tetra-di-t-butyl hydroxyhydrocinnamate, camellia sinensis leaf extract, glycine soja (soybean) sprout extract, perfluorodecalin, silk extract, hydrolyzed silk, perfluoromethylcyclopentane, silica, steareth-20, citric acid, saccharum officinarum (sugarcane) extract, cocos nucifera (coconut) fruit extract, hydrolyzed collagen, saccharomyces/camellia sinensis extract ferment filtrate, bacillus/cordyceps sinensis/ganoderma lucidum/inonotus obliquus/lentinus edodes/phellinus linteus/schizophyllum commune/tricholoma matsutake extract ferment filtrate, phaseolus angularis seed extract, lactobacillus ferment, lactobacillus/centella asiatica/gleditsia sinensis thorn/houttuynia cordata extract/phellodendron amurense bark/polygonum cuspidatum root/prunella vulgaris/torilis japonica extract ferment filtrate, lactobacillus/rice ferment filtrate, sodium benzoate, chrysanthemum indicum flower extract, potassium sorbate, BHT, diamond powder, lactobacillus/honeysuckle flower/licorice root/morus alba root/pueraria lobata root/schisandra chinensis fruit/scutellaria baicalensis root/sophora japonica flower extract ferment filtrate, aloe barbadensis leaf extract, caprylhydroxamic acid, olea europaea (olive) leaf extract, artemisia princeps leaf extract, cinnamomum cassia bark extract, pueraria lobata root extract, diospyros kaki leaf extract, morus alba fruit extract, chlorhexidine digluconate, n-hydroxysuccinimide, biotin, thiamine HCL, niacin, folic acid, retinyl palmitate, carnitine HCL, riboflavin, tocopherol, ascorbic acid, pantothenic acid, sodium citrate, palmitoyl tripeptide-1, hydrolyzed hyaluronic acid, chrysin, palmitoyl tetrapeptide-7; may contain: titanium dioxide, iron oxides

Questions or comments?

Call 800-620-3956